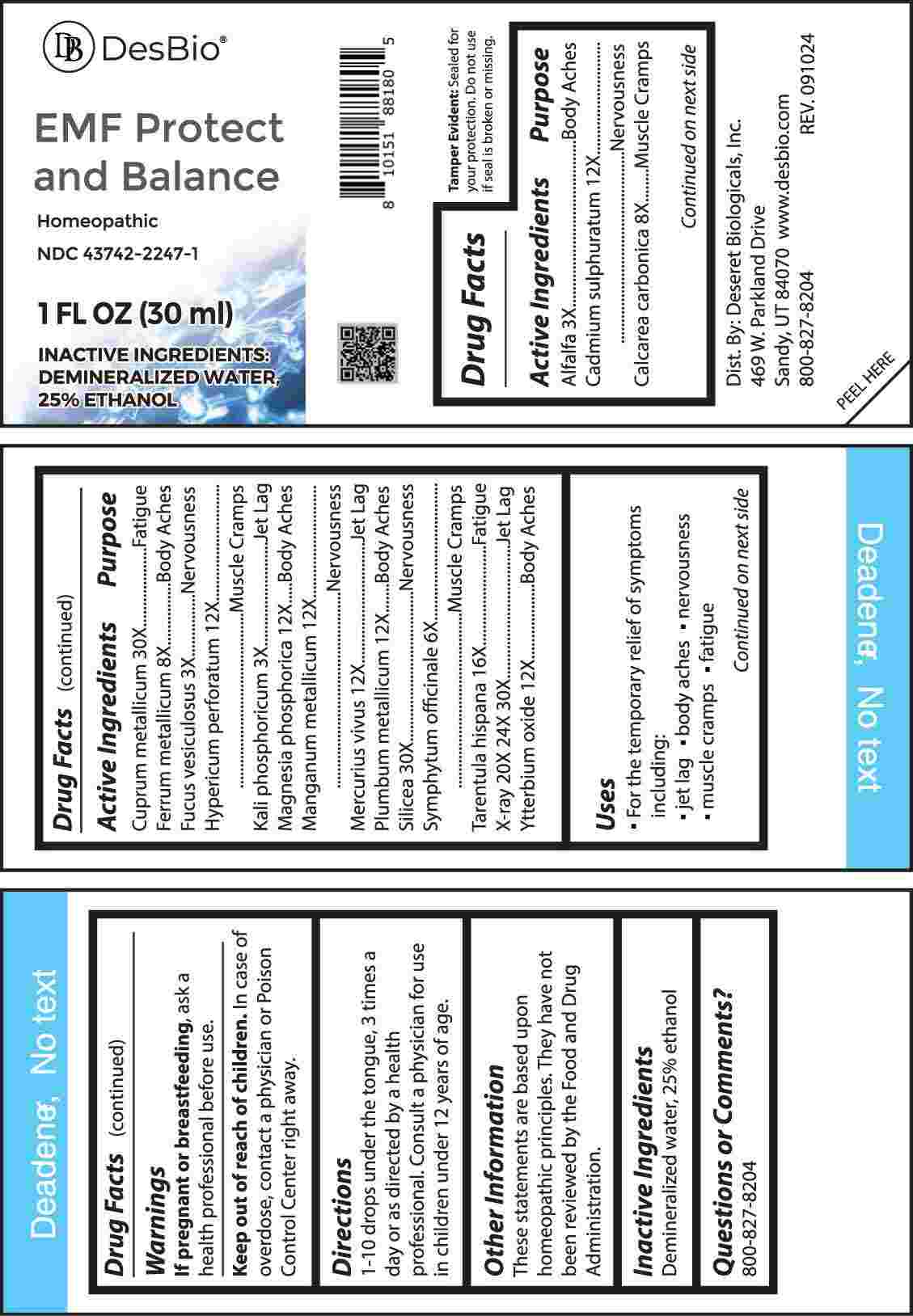 DRUG LABEL: EMF Protect and Balance
NDC: 43742-2247 | Form: LIQUID
Manufacturer: Deseret Biologicals, Inc.
Category: homeopathic | Type: HUMAN OTC DRUG LABEL
Date: 20250317

ACTIVE INGREDIENTS: MEDICAGO SATIVA WHOLE 3 [hp_X]/1 mL; CADMIUM SULFIDE 12 [hp_X]/1 mL; OYSTER SHELL CALCIUM CARBONATE, CRUDE 8 [hp_X]/1 mL; COPPER 30 [hp_X]/1 mL; IRON 8 [hp_X]/1 mL; FUCUS VESICULOSUS 3 [hp_X]/1 mL; HYPERICUM PERFORATUM WHOLE 12 [hp_X]/1 mL; DIBASIC POTASSIUM PHOSPHATE 3 [hp_X]/1 mL; MAGNESIUM PHOSPHATE, DIBASIC TRIHYDRATE 12 [hp_X]/1 mL; MANGANESE 12 [hp_X]/1 mL; MERCURY 12 [hp_X]/1 mL; LEAD 12 [hp_X]/1 mL; SILICON DIOXIDE 30 [hp_X]/1 mL; COMFREY ROOT 6 [hp_X]/1 mL; LYCOSA TARANTULA 16 [hp_X]/1 mL; ALCOHOL, X-RAY EXPOSED (1000 RAD) 20 [hp_X]/1 mL; YTTERBIUM OXIDE 12 [hp_X]/1 mL
INACTIVE INGREDIENTS: WATER; ALCOHOL

DRUG FACTS:

ACTIVE INGREDIENT:

Alfalfa 3X, Cadmium Sulphuratum 12X, Calcarea Carbonica 8X, Cuprum Metallicum 30X, Ferrum Metallicum 8X, Fucus Vesiculosus 3X, Hypericum Perforatum 12X, Kali Phosphoricum 3X, Magnesia Phosphorica 12X, Manganum Metallicum 12X, Mercurius Vivus 12X, Plumbum Metallicum 12X, Silicea 30X, Symphytum Officinale 6X, Tarentula Hispana 16X, X-Ray 20X, 24X, 30X, Ytterbium Oxide 12X.

PURPOSE:

Alfalfa – Body Aches, Cadmium Sulphuratum - Nervousness, Calcarea Carbonica – Muscle Cramps, Cuprum Metallicum - Fatigue, Ferrum Metallicum – Body Aches, Fucus Vesiculosus - Nervousness, Hypericum Perforatum – Muscle Cramps, Kali Phosphoricum – Jet Lag, Magnesia Phosphorica – Body Aches, Manganum Metallicum - Nervousness, Mercurius Vivus – Jet Lag, Plumbum Metallicum – Body Aches, Silicea - Nervousness, Symphytum Officinale – Muscle Cramps, Tarentula Hispana - Fatigue, X-Ray – Jet Lag, Ytterbium Oxide – Body Aches

USES:

• For the temporary relief of symptoms including:

• jet lag • body aches • nervousness

• muscle cramps • fatigue

These statements are based upon homeopathic principles. They have not been reviewed by the Food and Drug Administration.

WARNINGS:

If pregnant or breastfeeding, ask a health professional before use.

Keep out of reach of children. In case of overdose, contact a physician or Poison Control Center right away.

Tamper Evident: Sealed for your protection. Do not use if seal is broken or missing.

KEEP OUT OF REACH OF CHILDREN:

In case of overdose, contact a physician or Poison Control Center right away.

DIRECTIONS:

1-10 drops under the tongue, 3 times a day or as directed by a health professional. Consult a physician for use in children under 12 years of age.

INACTIVE INGREDIENTS:

Demineralized water, 25% ethanol

QUESTIONS:

Dist. By: Deseret Biologicals, Inc.
469 W. Parkland Drive
Sandy, UT 84070

www.desbio.com

800-827-8204

PACKAGE LABEL DISPLAY:

DesBio

EMF Protect

and Balance

Homeopathic

NDC 43742-2247-1

1 FL OZ (30 ml)